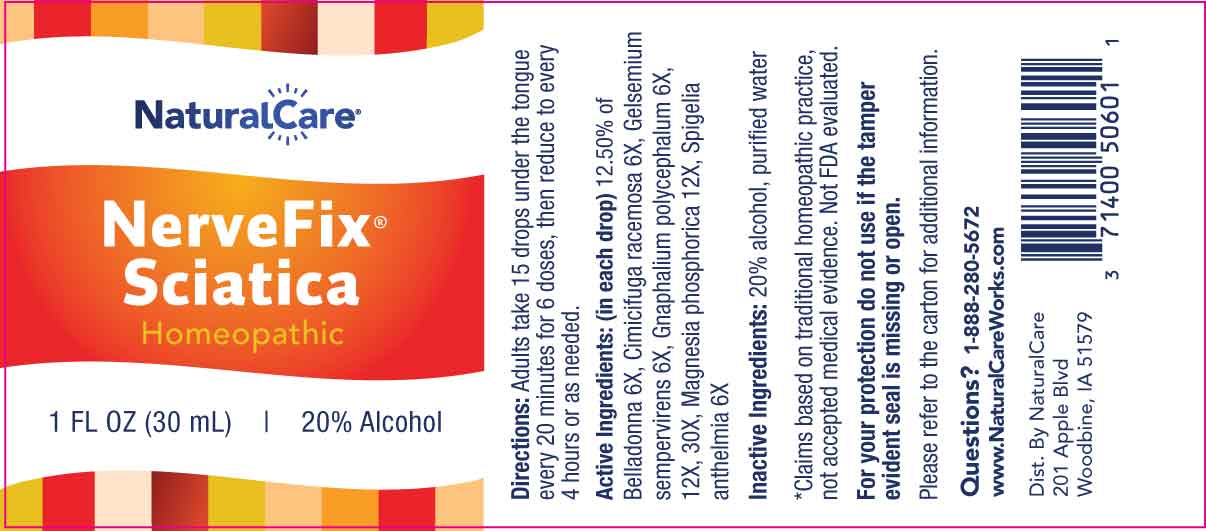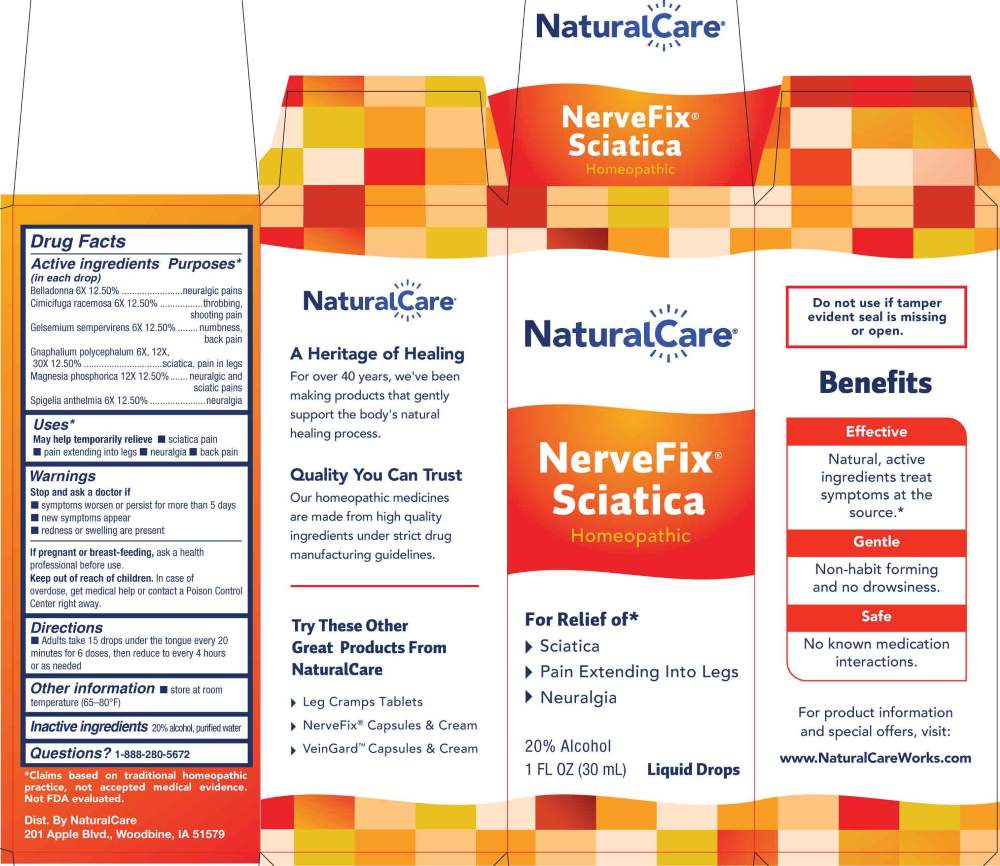 DRUG LABEL: NerveFix Sciatica
NDC: 70163-0012 | Form: LIQUID
Manufacturer: NaturalCare
Category: homeopathic | Type: HUMAN OTC DRUG LABEL
Date: 20260203

ACTIVE INGREDIENTS: ATROPA BELLADONNA 6 [hp_X]/1 mL; BLACK COHOSH 6 [hp_X]/1 mL; GELSEMIUM SEMPERVIRENS ROOT 6 [hp_X]/1 mL; SPIGELIA ANTHELMIA WHOLE 6 [hp_X]/1 mL; PSEUDOGNAPHALIUM OBTUSIFOLIUM WHOLE 6 [hp_X]/1 mL; MAGNESIUM PHOSPHATE, DIBASIC TRIHYDRATE 12 [hp_X]/1 mL
INACTIVE INGREDIENTS: WATER; ALCOHOL

DRUG FACTS:

ACTIVE INGREDIENT:

(in each drop) 12.50% of Belladonna 6X, Cimicifuga Racemosa 6X, Gelsemium Sempervirens 6X, Gnaphalium Polycephalum 6X, 12X, 30X, Magnesia Phosphorica 12X, Spigelia Anthelmia 6X.

PURPOSE:

Belladonna – neuralgic pains, Cimicifuga Racemosa – throbbing, shooting pain, Gelsemium Sempervirens – numbness, back pain, Gnaphalium Polycephalum – Sciatica, pain in legs, Magnesia Phosphorica – Neuralgic and sciatic pains, Spigelia Anthelmia – Neuralgia*

*Claims based on traditional homeopathic practice, not accepted medical evidence. Not FDA evaluated.

USES:

May help temporarily relieve

■ sciatica pain ■ pain extending into legs ■ neuralgia ■ back pain

*Claims based on traditional homeopathic practice, not accepted medical evidence. Not FDA evaluated.

WARNINGS:

Stop use and ask a doctor if

■ symptoms worsen or persist for more than 5 days

■ new symptoms appear

■ redness or swelling are present

If pregnant or breast-feeding, ask a health professional before use.

Keep out of reach of children. In case of overdose, get medical help or contact a Poison Control Center right away.

Do not use if tamper evident seal is missing or open.

■ Store at room temperature (65-80ºF)

KEEP OUT OF REACH OF CHILDREN:

In case of overdose, get medical help or contact a Poison Control Center right away.

DIRECTIONS:

■ Adults take 15 drops under the tongue every 20 minutes for 6 doses, then reduce to every 4 hours or as needed

INACTIVE INGREDIENTS:

20% alcohol, purified water

QUESTIONS:

Dist. By NaturalCare

201 Apple Blvd.

Woodbine, IA 51579

www.NaturalCareWorks.com

1-888-280-5672

PACKAGE LABEL DISPLAY:

NaturalCare

NerveFix Sciatica

Homeopathic

1 FL OZ (30 mL)